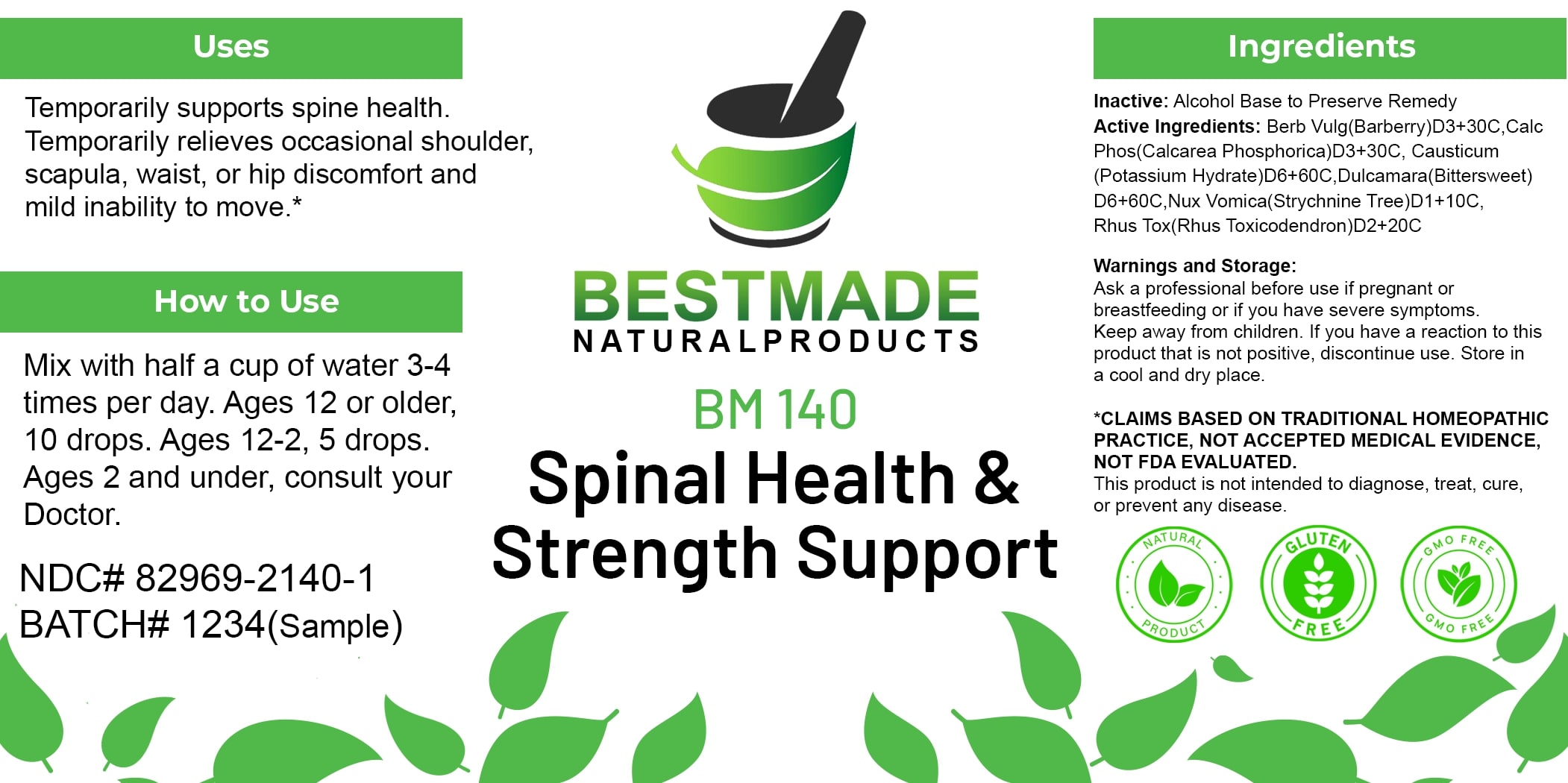 DRUG LABEL: Bestmade Natural Products BM140
NDC: 82969-2140 | Form: LIQUID
Manufacturer: Bestmade Natural Products
Category: homeopathic | Type: HUMAN OTC DRUG LABEL
Date: 20250214

ACTIVE INGREDIENTS: CAUSTICUM 30 [hp_C]/30 [hp_C]; STRYCHNOS NUX-VOMICA SEED 30 [hp_C]/30 [hp_C]; BERBERIS VULGARIS ROOT BARK 30 [hp_C]/30 [hp_C]; TOXICODENDRON PUBESCENS LEAF 30 [hp_C]/30 [hp_C]; SOLANUM DULCAMARA TOP 30 [hp_C]/30 [hp_C]; TRIBASIC CALCIUM PHOSPHATE 30 [hp_C]/30 [hp_C]
INACTIVE INGREDIENTS: ALCOHOL 30 [hp_C]/30 [hp_C]

BM140

DOSAGE AND ADMINISTRATION

How to Use

Mix with half a cup of water 3-4 times per day. Ages 12 or older, 10 drops. Ages 12-2, 5 drops. Ages 2 and under, consult your Doctor.

INACTIVE INGREDIENT

Ingredients

Inactive: Alcohol Base to Preserve Remedy

ACTIVE INGREDIENT

Active Ingredients: Berb Vulg(Barberry)D3+30C, Calc Phos(Calcarea Phosphorica)D3+30C, Causticum (Potassium Hydrate)D6+60C, Dulcamara(Bittersweet) D6+60C, Nux Vomica(Strychnine Tree)D1+10C, Rhus Tox (Rhus Toxicodendron)D2+20C

Uses

Temporarily supports spine health. Temporarily relieves occasional shoulder, scapula, waist, or hip discomfort and mild inability to move.*

*CLAIMS BASED ON TRADITIONAL HOMEOPATHIC PRACTICE, NOT ACCEPTED MEDICAL EVIDENCE. NOT FDA EVALUATED.

This product is not intended to diagnose, treat, cure, or prevent any disease.

Uses

Temporarily supports spine health. Temporarily relieves occasional shoulder, scapula, waist, or hip discomfort and mild inability to move.*

*CLAIMS BASED ON TRADITIONAL HOMEOPATHIC PRACTICE, NOT ACCEPTED MEDICAL EVIDENCE. NOT FDA EVALUATED.

This product is not intended to diagnose, treat, cure, or prevent any disease.

KEEP OUT OF REACH OF CHILDREN

Warnings and Storage:

Ask a professional before use if pregnant or breastfeeding or if you have severe symptoms. Keep away from children. If you have a reaction to this product that is not positive, discontinue use. Store in a cool and dry place.

Warnings and Storage:

Ask a professional before use if pregnant or breastfeeding or if you have severe symptoms. Keep away from children. If you have a reaction to this product that is not positive, discontinue use. Store in a cool and dry place.

*CLAIMS BASED ON TRADITIONAL HOMEOPATHIC PRACTICE, NOT ACCEPTED MEDICAL EVIDENCE. NOT FDA EVALUATED.

This product is not intended to diagnose, treat, cure, or prevent any disease.

Entire package label